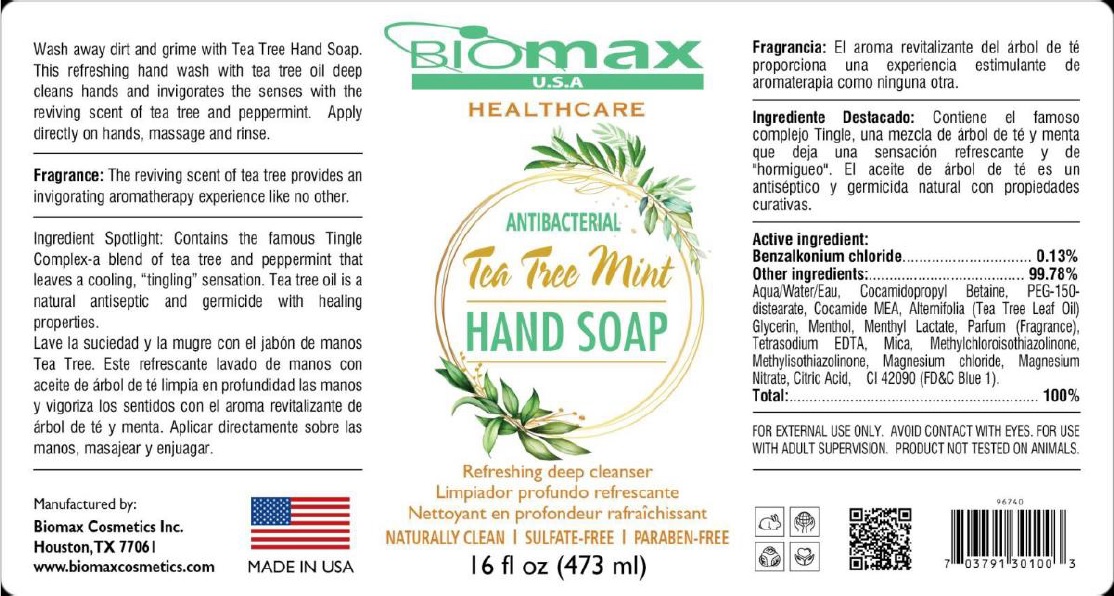 DRUG LABEL: Biomax USA ANTIBACTERIAL HAND WASH
NDC: 77369-905 | Form: SOAP
Manufacturer: Biomax Cosmetics
Category: otc | Type: HUMAN OTC DRUG LABEL
Date: 20200728

ACTIVE INGREDIENTS: BENZALKONIUM CHLORIDE 0.13 g/100 mL
INACTIVE INGREDIENTS: WATER; COCAMIDOPROPYL BETAINE; PEG-150 DISTEARATE; COCO MONOETHANOLAMIDE; TEA LEAF OIL; GLYCERIN; MENTHOL, UNSPECIFIED FORM; MENTHYL LACTATE, (-)-; EDETATE SODIUM; MICA; METHYLCHLOROISOTHIAZOLINONE; METHYLISOTHIAZOLINONE; MAGNESIUM CHLORIDE; MAGNESIUM NITRATE; CITRIC ACID MONOHYDRATE; FD&C BLUE NO. 1

Biomax ANTIBACTERIAL Tea Tree Mint HAND SOAP

Active ingredient:

Benzalkonium chloride..........0.13%

Purpose

Antibacterial

Other ingredients:..............99.78%

Aqua/Water/Eau, Cocamidopropyl Betaine, PEG-150-distearate, Cocamide MEA, Alternifolia (Tea Tree Leaf Oil), Glycerin, Menthol, Menthyl Lactate, Parfum (Fragrance), Tetrasodium EDTA, Mica, Methylchloroisothiazolinone, Methylisothiazolinone, Magnesium chloride, Magnesium Nitrate, Citric Acid, CI 42090 (FD&C Blue 1).

Uses

• hand sanitizer to decrease bacteria on the skin
• recommended for repeated use

Warnings

FOR EXTERNAL USE ONLY. AVOID CONTACT WITH EYES. FOR USE WITH ADULT SUPERVISION. PRODUCT NOT TESTED ON ANIMALS.

Keep out of reach of children. If swallowed, get medical help or contact a Poison Control Center right away.

Directions

Apply directly on hands, massage and rinse.

HEALTHCARE

Refreshing deep cleanser

NATURALLY CLEAN | SULFATE-FREE | PARABEN-FREE

Wash away dirt and grime with Tea Tree Hand Soap. This refreshing hand wash with tea tree oil deep cleans hands and invigorates the senses with the reviving scent of tea tree and peppermint.

Fragrance: The reviving scent of tea tree provides an invigorating aromatherapy experience like no other.

Ingredient Spotlight: Contains the famous Tingle Complex-a blend of tea tree and peppermint that leaves a cooling, "tingling" sensation. Tea tree oil is a natural antiseptic and germicide with healing properties.

Manufactured by:

Biomax Cosmetics Inc.

Houston, TX

www.biomaxcosmetics.com

MADE IN USA